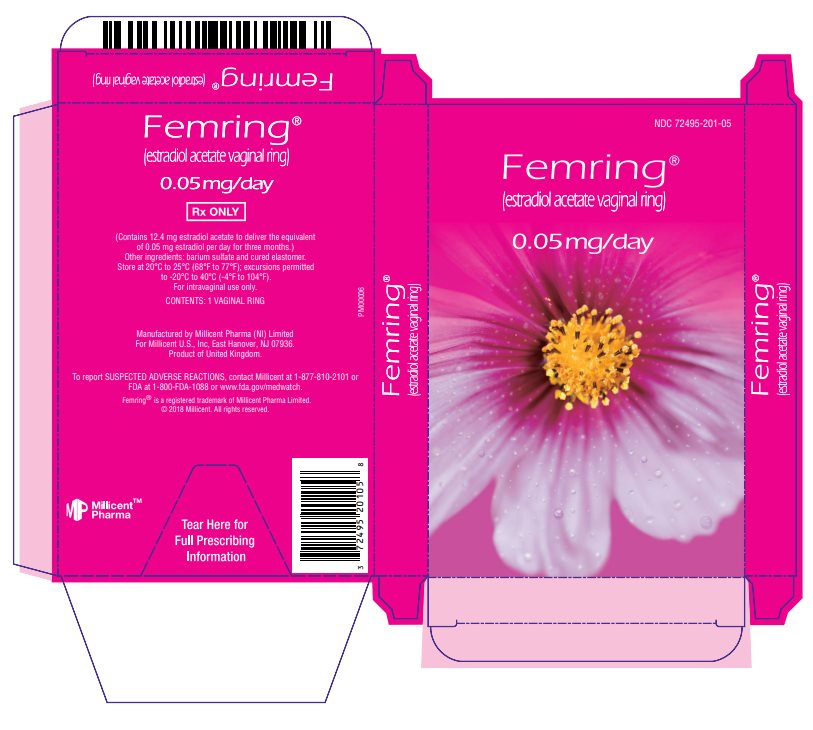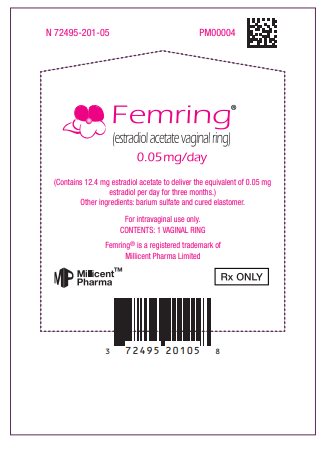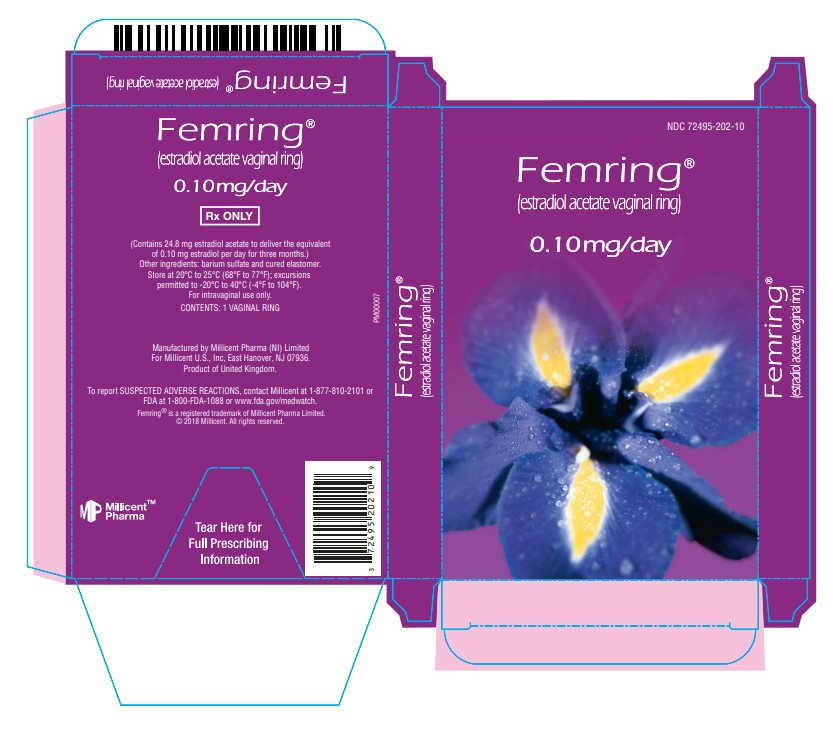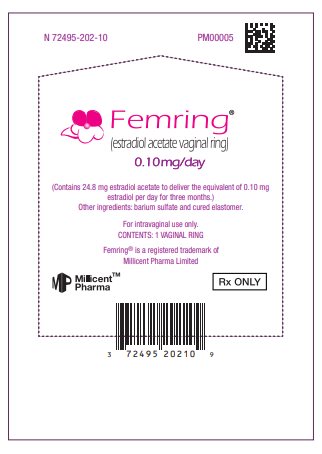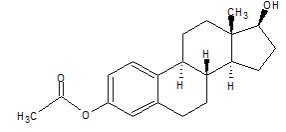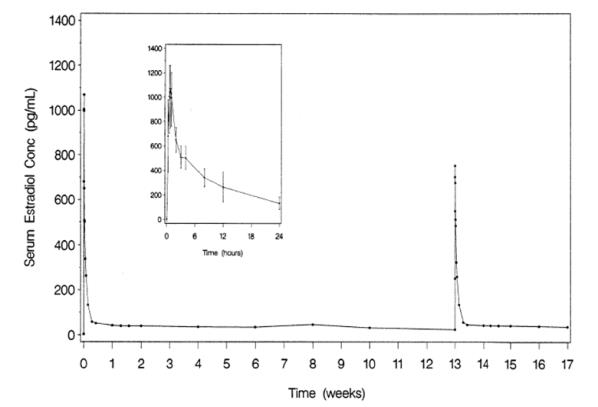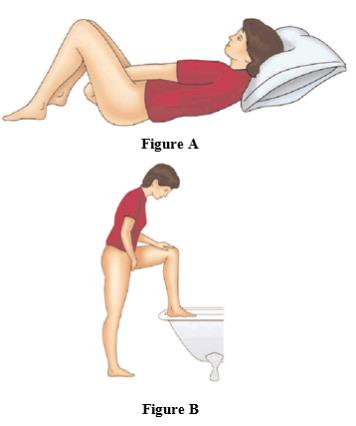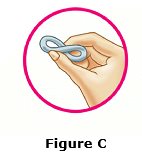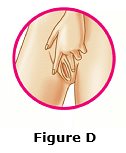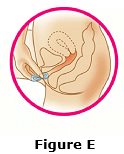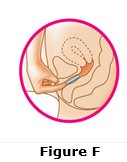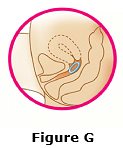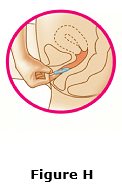 DRUG LABEL: Femring
NDC: 72495-201 | Form: RING
Manufacturer: Millicent US, Inc.
Category: prescription | Type: HUMAN PRESCRIPTION DRUG LABEL
Date: 20251209

ACTIVE INGREDIENTS: ESTRADIOL ACETATE 0.05 mg/1 d
INACTIVE INGREDIENTS: DIMETHICONE, UNSPECIFIED; DIATOMACEOUS EARTH; STANNOUS 2-ETHYLHEXANOATE; TETRAPROPYL ORTHOSILICATE; BARIUM SULFATE

HIGHLIGHTS OF PRESCRIBING INFORMATION

These highlights do not include all the information needed to use FEMRING safely and effectively. See Full Prescribing Information for FEMRING.
Femring® (estradiol acetate vaginal ring)
Initial U.S. Approval: 1975

RECENT MAJOR CHANGES

Warnings and Precautions, Malignant Neoplasms (5.2) 11/2023

WARNING: ENDOMETRIAL CANCER, CARDIOVASCULAR DISORDERS, BREAST CANCER AND PROBABLE DEMENTIA

See full prescribing information for complete boxed warning.

Estrogen-Alone Therapy

- There is an increased risk of endometrial cancer in a woman with a uterus who uses unopposed estrogens (5.2)
- Estrogen-alone therapy should not be used for the prevention of cardiovascular disease or dementia (5.1, 5.3)
- The Women’s Health Initiative (WHI) estrogen-alone substudy reported increased risks of stroke and deep vein thrombosis (DVT) (5.1)
- The WHI Memory Study (WHIMS) estrogen-alone ancillary study of WHI reported an increased risk of probable dementia in postmenopausal women 65 years of age and older (5.3)

Estrogen Plus Progestin Therapy

- Estrogen plus progestin therapy should not be used for the prevention of cardiovascular disease or dementia (5.1, 5.3)
- The WHI estrogen plus progestin substudy reported increased risks of stroke, DVT, pulmonary embolism (PE), and myocardial infarction (MI) (5.1)
- The WHI estrogen plus progestin substudy reported an increased risk of invasive breast cancer (5.2)
- The WHIMS estrogen plus progestin ancillary study of WHI reported an increased risk of probable dementia in postmenopausal women 65 years of age and older (5.3)

1 INDICATIONS AND USAGE

Femring is an estrogen indicated for:

- Treatment of Moderate to Severe Vasomotor Symptoms due to Menopause (1.1)
- Treatment of Moderate to Severe Vulvar and Vaginal Atrophy due to Menopause (1.2)

2 DOSAGE AND ADMINISTRATION

- One ring inserted into the vagina for 3 months. Patients should be started at the lowest dose. (2.1, 2.2)

3 DOSAGE FORMS AND STRENGTHS

- Femring (0.05 mg/day): Each off-white, soft, flexible ring has a central core that contains 12.4 mg of estradiol acetate, which releases at a rate equivalent to 0.05 mg of estradiol per day for 3 months. (3)
- Femring (0.10 mg/day): Each off-white, soft, flexible ring has a central core that contains 24.8 mg of estradiol acetate, which releases at a rate equivalent to 0.10 mg of estradiol per day for 3 months. (3)

4 CONTRAINDICATIONS

- Undiagnosed abnormal genital bleeding (4)
- Known, suspected, or history of breast cancer (4, 5.2)
- Known or suspected estrogen-dependent neoplasia (4, 5.2)
- Active DVT, PE, or history of these conditions (4, 5.1)
- Active arterial thromboembolic disease (for example, stroke and MI), or a history of these conditions (4, 5.1)
- Known anaphylactic reaction or angioedema to Femring (4)
- Known liver impairment or disease (4, 5.10)
- Known protein C, protein S, or antithrombin deficiency, or other known thrombophilic disorders (4)
- Known or suspected pregnancy (4, 8.1)

5 WARNINGS AND PRECAUTIONS

- Estrogens increase the risk of gallbladder disease (5.4)
- Discontinue estrogen if severe hypercalcemia, loss of vision, severe hypertriglyceridemia or cholestatic jaundice occurs (5.5, 5.6, 5.9, 5.10)
- Monitor thyroid function in women on thyroid replacement therapy (5.11, 5.18)

6 ADVERSE REACTIONS

Most common adverse reactions (incidence > 5 percent) are vaginal bleeding and breast tenderness. (6.1)

To report SUSPECTED ADVERSE REACTIONS, contact Millicent at 1-877-810-2101 or FDA at 1-800-FDA-1088 or www.fda.gov/medwatch.

7 DRUG INTERACTIONS

- Inducers and/or inhibitors of CYP3A4 may affect estrogen drug metabolism (7.1)

8 USE IN SPECIFIC POPULATIONS

- Nursing Mothers: Estrogen administration to nursing women has been shown to decrease the quantity and quality of breast milk (8.3)
- Geriatric Use: An increased risk of probable dementia in women over 65 years of age was reported in the Women’s Health Initiative Memory ancillary studies of the Women’s Health Initiative (5.3, 8.5)

FULL PRESCRIBING INFORMATION

WARNING: ENDOMETRIAL CANCER, CARDIOVASCULAR DISORDERS, BREAST CANCER AND PROBABLE DEMENTIA

Estrogen-Alone Therapy

Endometrial Cancer

There is an increased risk of endometrial cancer in a woman with a uterus who uses unopposed estrogens. Adding a progestin to estrogen therapy has been shown to reduce the risk of endometrial hyperplasia, which may be a precursor to endometrial cancer. Adequate diagnostic measures, including directed or random endometrial sampling when indicated, should be undertaken to rule out malignancy in postmenopausal women with undiagnosed persistent or recurring abnormal genital bleeding [see Warnings and Precautions (5.2)].

Cardiovascular Disorders and Probable Dementia

Estrogen-alone therapy should not be used for the prevention of cardiovascular disease or dementia [see Warnings and Precautions (5.1, 5.3), and Clinical Studies (14.3, 14.4)].

The Women’s Health Initiative (WHI) estrogen-alone substudy reported increased risks of stroke and deep vein thrombosis (DVT) in postmenopausal women (50 to 79 years of age) during 7.1 years of treatment with daily oral conjugated estrogens (CE) [0.625 mg]-alone, relative to placebo [see Warnings and Precautions (5.1), and Clinical Studies (14.3)].

The WHI Memory Study (WHIMS) estrogen-alone ancillary study of the WHI reported an increased risk of developing probable dementia in postmenopausal women 65 years of age or older during 5.2 years of treatment with daily CE (0.625 mg)-alone, relative to placebo. It is unknown whether this finding applies to younger postmenopausal women [see Warnings and Precautions (5.3), Use in Specific Populations (8.5), and Clinical Studies (14.4)].

In the absence of comparable data, these risks should be assumed to be similar for other doses of CE and other dosage forms of estrogens.

Estrogens with or without progestins should be prescribed at the lowest effective doses and for the shortest duration consistent with treatment goals and risks for the individual woman.

Estrogen Plus Progestin Therapy

Cardiovascular Disorders and Probable Dementia

Estrogen plus progestin therapy should not be used for the prevention of cardiovascular disease or dementia [see Warnings and Precautions (5.1, 5.3) and Clinical Studies (14.3, 14.4)].

The WHI estrogen plus progestin substudy reported increased risks of DVT, pulmonary embolism (PE), stroke and myocardial infarction (MI) in postmenopausal women (50 to 79 years of age) during 5.6 years of treatment with daily oral CE (0.625 mg) combined with medroxyprogesterone acetate (MPA) [2.5 mg], relative to placebo [see Warnings and Precautions (5.1), and Clinical Studies (14.3)].

The WHIMS estrogen plus progestin ancillary study of the WHI reported increased risk of developing probable dementia in postmenopausal women 65 years of age or older during 4 years of treatment with daily CE (0.625 mg) combined with MPA (2.5 mg), relative to placebo. It is unknown whether this finding applies to younger postmenopausal women [see Warnings and Precautions (5.3), Use in Specific Populations (8.5) and Clinical Studies (14.4)].

Breast Cancer

The WHI estrogen plus progestin substudy also demonstrated an increased risk of invasive breast cancer [see Warnings and Precautions (5.3), and Clinical Studies (14.3)].

In the absence of comparable data, these risks should be assumed to be similar for other doses of CE and MPA and other combinations and dosage forms of estrogens and progestins.

Estrogens with or without progestins should be prescribed at the lowest effective doses and for the shortest duration consistent with treatment goals and risks for the individual woman.

2 DOSAGE AND ADMINISTRATION

Generally, when estrogen is prescribed for a postmenopausal woman with a uterus, a progestin should also be considered to reduce the risk of endometrial cancer.

A woman without a uterus does not need a progestin. In some cases, however, hysterectomized women with a history of endometriosis may need a progestin [see Warnings and Precautions (5.2, 5.14)].

Use of estrogen-alone, or in combination with a progestin, should be with the lowest effective dose and for the shortest duration consistent with treatment goals and risks for the individual woman. Postmenopausal women should be re-evaluated periodically as clinically appropriate to determine if treatment is still necessary.

2.1 Treatment of Moderate to Severe Vasomotor Symptoms due to Menopause

Start therapy with 0.05 mg/day. Dosage adjustment should be guided by the clinical response.

Therapy should be started at the lowest effective dose and the shortest duration consistent with treatment goals. Attempts to taper or discontinue the medication should be made at 3 to 6 month intervals.

2.2 Treatment of Moderate to Severe Vulvar and Vaginal Atrophy due to Menopause.

Start therapy with 0.05 mg/day. Dosage adjustment should be guided by the clinical response.

Therapy should be started at the lowest effective dose and the shortest duration consistent with treatment goals. Attempts to taper or discontinue the medication should be made at 3 to 6 month intervals.

3 DOSAGE FORMS AND STRENGTHS

The following two strengths of Femring are available:

Femring (0.05 mg/day): Each off-white, soft, flexible ring has a central core that contains 12.4 mg of estradiol acetate, which releases at a rate equivalent to 0.05 mg of estradiol per day for 3 months.

Femring (0.10 mg/day): Each off-white, soft, flexible ring has a central core that contains 24.8 mg of estradiol acetate, which releases at a rate equivalent to 0.10 mg of estradiol per day for 3 months.

4 CONTRAINDICATIONS

Femring is contraindicated in women with any of the following conditions:

- Undiagnosed abnormal genital bleeding
- Known, suspected, or history of breast cancer
- Known or suspected estrogen-dependent neoplasia
- Active DVT, PE, or history of these conditions
- Active arterial thromboembolic disease (for example, stroke and MI), or a history of these conditions
- Known anaphylactic reaction or angioedema to Femring
- Known liver impairment or disease
- Known protein C, protein S, or antithrombin deficiency, or other known thrombophilic disorders
- Known or suspected pregnancy

5 WARNINGS AND PRECAUTIONS

Femring is used only in the vagina, however, the risks associated with oral estrogens should be taken into account.

5.1 Cardiovascular Disorders

An increased risk of stroke and DVT has been reported with estrogen-alone therapy. An increased risk of PE, DVT, stroke, and MI has been reported with estrogen plus progestin therapy. Should any of these occur or be suspected, estrogen with or without progestin therapy should be discontinued immediately.

Risk factors for arterial vascular disease (for example, hypertension, diabetes mellitus, tobacco use, hypercholesterolemia, and obesity) and/or venous thromboembolism (VTE) (for example, personal history or family history of VTE, obesity, and systemic lupus erythematosus) should be managed appropriately.

Stroke

In the WHI estrogen-alone substudy, a statistically significant increased risk of stroke was reported in women 50 to 79 years of age receiving daily CE (0.625 mg)-alone compared to women in the same age group receiving placebo (45 versus 33 per 10,000 women-years). The increase in risk was demonstrated in year 1 and persisted [see Clinical Studies (14.3)]. Should a stroke occur or be suspected, estrogen-alone therapy should be discontinued immediately.

Subgroup analyses of women 50 to 59 years of age suggest no increased risk of stroke for those women receiving CE (0.625 mg)-alone versus those receiving placebo (18 versus 21 per 10,000 women-years).^1

In the WHI estrogen plus progestin substudy, a statistically significant increased risk of stroke was reported in women 50 to 79 years of age receiving daily CE (0.625 mg) plus MPA (2.5 mg) compared to women in the same age group receiving placebo (33 versus 25 per 10,000 women-years) [see Clinical Studies (14.3)]. The increase in risk was demonstrated after the first year and persisted.^1 Should a stroke occur or be suspected, estrogen plus progestin therapy should be discontinued immediately.

Coronary Heart Disease

In the WHI estrogen-alone substudy, no overall effect on coronary heart disease (CHD) events (defined as nonfatal MI, silent MI, or CHD death) was reported in women receiving estrogen-alone compared to placebo^2 [see Clinical Studies (14.3)].

Subgroup analyses of women 50 to 59 years of age suggest a statistically non-significant reduction in CHD events (CE [0.625 mg]-alone compared to placebo) in women with less than 10 years since menopause (8 versus 16 per 10,000 woman-years).^1

In the WHI estrogen plus progestin substudy, there was a statistically non-significant increased risk of CHD events reported in women receiving daily CE (0.625 mg) plus MPA (2.5 mg) compared to women receiving placebo (41 versus 34 per 10,000 women-years).^1 An increase in relative risk was demonstrated in year 1, and a trend toward decreasing relative risk was reported in years 2 through 5 [see Clinical Studies (14.3)].

In postmenopausal women with documented heart disease (n = 2,763, average 66.7 years of age), in a controlled clinical trial of secondary prevention of cardiovascular disease (Heart and Estrogen/Progestin Replacement Study; HERS) treatment with daily CE (0.625 mg) plus MPA (2.5 mg) demonstrated no cardiovascular benefit. During an average follow-up of 4.1 years, treatment with CE plus MPA did not reduce the overall rate of CHD events in postmenopausal women with established CHD. There were more CHD events in the CE plus MPA-treated group than in the placebo group in year 1, but not during the subsequent years. Two thousand, three hundred and twenty-one (2,321) women from the original HERS trial agreed to participate in an open label extension of HERS, HERS II. Average follow-up in HERS II was an additional 2.7 years, for a total of 6.8 years overall. Rates of CHD events were comparable among women in the CE plus MPA group and the placebo group in HERS, HERS II, and overall.

Venous Thromboembolism

In the WHI estrogen-alone substudy, the risk of VTE (DVT and PE), was increased for women receiving daily CE (0.625 mg)-alone compared to placebo (30 versus 22 per 10,000 women-years), although only the increased risk of DVT reached statistical significance (23 versus 15 per 10,000 women-years). The increase in VTE risk was demonstrated during the first 2 years^3 [see Clinical Studies (14.3)]. Should a VTE occur or be suspected, estrogen-alone therapy should be discontinued immediately.

In the WHI estrogen plus progestin substudy, a statistically significant 2-fold greater rate of VTE was reported in women receiving daily CE (0.625 mg) plus MPA (2.5 mg) compared to women receiving placebo (35 versus 17 per 10,000 women-years). Statistically significant increases in risk for both DVT (26 versus 13 per 10,000 women-years) and PE (18 versus 8 per 10,000 women-years) were also demonstrated. The increase in VTE risk was demonstrated during the first year and persisted^4 [see Clinical Studies (14.3)]. Should a VTE occur or be suspected, estrogen plus progestin therapy should be discontinued immediately.

If feasible, estrogens should be discontinued at least 4 to 6 weeks before surgery of the type associated with an increased risk of thromboembolism, or during periods of prolonged immobilization.

5.2 Malignant Neoplasms

Endometrial Cancer

An increased risk of endometrial cancer has been reported with the use of unopposed estrogen therapy in a woman with a uterus. The reported endometrial cancer risk among unopposed estrogen users is about 2 to 12 times greater than in non-users, and appears dependent on duration of treatment and on estrogen dose. Most studies show no significant increased risk associated with use of estrogens for less than 1 year. The greatest risk appears associated with prolonged use, with increased risks of 15- to 24-fold for 5 to 10 years or more. This risk has been shown to persist for at least 8 to 15 years after estrogen therapy is discontinued.

Clinical surveillance of all women using estrogen-alone or estrogen plus progestin therapy is important. Adequate diagnostic measures, including directed or random endometrial sampling when indicated, should be undertaken to rule out malignancy in postmenopausal women with undiagnosed persistent or recurring abnormal genital bleeding.

There is no evidence that the use of natural estrogens results in a different endometrial risk profile than synthetic estrogens of equivalent estrogen dose. Adding a progestin to estrogen therapy in postmenopausal women has been shown to reduce the risk of endometrial hyperplasia, which may be a precursor to endometrial cancer.

Breast Cancer

The WHI substudy of daily CE (0.625 mg)-alone provided information about breast cancer in estrogen-alone users. In the WHI estrogen-alone substudy, after an average follow up of 7.1 years, daily CE-alone was not associated with an increased risk of invasive breast cancer (relative risk [RR] 0.80)^5 [see Clinical Studies (14.3)].

After a mean follow-up of 5.6 years, the estrogen plus progestin substudy reported an increased risk of invasive breast cancer in women who took daily CE plus MPA. In this substudy, prior use of estrogen-alone or estrogen plus progestin therapy was reported by 26 percent of the women. The relative risk of invasive breast cancer was 1.24, and the absolute risk was 41 versus 33 cases per 10,000 women-years for CE plus MPA compared with placebo. Among women who reported prior use of hormone therapy, the relative risk of invasive breast cancer was 1.86 and the absolute risk was 46 versus 25 cases per 10,000 women-years for CE plus MPA compared with placebo. Among women who reported no prior use of hormone therapy, the relative risk of invasive breast cancer was 1.09, and the absolute risk was 40 versus 36 cases per 10,000 women-years for CE plus MPA compared with placebo. In the same substudy, invasive breast cancers were larger, were more likely to be node positive, and were diagnosed at a more advanced stage in the CE (0.625 mg) plus MPA (2.5 mg) group compared with the placebo group. Metastatic disease was rare with no apparent difference between the two groups. Other prognostic factors, such as histologic subtype, grade and hormone receptor status did not differ between the groups^6 [see Clinical Studies (14.3)].

Consistent with the WHI clinical trial, observational studies have also reported an increased risk of breast cancer for estrogen plus progestin therapy, and a smaller increased risk for estrogen-alone therapy, after several years of use. One large meta-analysis of prospective cohort studies reported increased risks that were dependent upon duration of use and could last up to >10 years after discontinuation of estrogen plus progestin therapy and estrogen-alone therapy. Extension of the WHI trials also demonstrated increased breast cancer risk associated with estrogen plus progestin therapy. Observational studies also suggest that the risk of breast cancer was greater, and became apparent earlier, with estrogen plus progestin therapy as compared to estrogen-alone therapy. However, these studies have not found significant variation in the risk of breast cancer among different estrogen plus progestin combinations, doses, or routes of administration.

The use of estrogen-alone and estrogen plus progestin has been reported to result in an increase in abnormal mammograms requiring further evaluation.

All women should receive yearly breast examinations by a healthcare provider and perform monthly breast self-examinations. In addition, mammography examinations should be scheduled based on patient age, risk factors and prior mammogram results.

Ovarian Cancer

The WHI estrogen plus progestin substudy reported a statistically non-significant increased risk of ovarian cancer. After an average follow-up of 5.6 years, the relative risk for ovarian cancer for CE plus MPA versus placebo was 1.58 (95 percent CI, 0.77-3.24). The absolute risk for CE plus MPA versus placebo was 4 versus 3 cases per 10,000 women-years.^7

A meta-analysis of 17 prospective and 35 retrospective epidemiology studies found that women who used hormonal therapy for menopausal symptoms had an increased risk for ovarian cancer. The primary analysis, using case-control comparisons, included 12,110 cancer cases from the 17 prospective studies. The relative risks associated with current use of hormonal therapy was 1.41 (95% confidence interval [CI] 1.32 to 1.50); there was no difference in the risk estimates by duration of the exposure (less than 5 years [median of 3 years] vs. greater than 5 years [median of 10 years] of use before the cancer diagnosis). The relative risk associated with combined current and recent use (discontinued use within 5 years before cancer diagnosis) was 1.37 (95% CI 1.27-1.48), and the elevated risk was significant for both estrogen-alone and estrogen plus progestin products. The exact duration of hormone therapy use associated with an increased risk of ovarian cancer, however, is unknown.

5.3 Probable Dementia

In the WHIMS estrogen-alone ancillary study of WHI, a population of 2,947 hysterectomized women 65 to 79 years of age was randomized to daily CE (0.625 mg)-alone or placebo.

After an average follow-up of 5.2 years, 28 women in the estrogen-alone group and 19 women in the placebo group were diagnosed with probable dementia. The relative risk of probable dementia for CE-alone versus placebo was 1.49 (95 percent CI, 0.83-2.66). The absolute risk of probable dementia for CE-alone versus placebo was 37 versus 25 cases per 10,000 women-years^8 [see Use in Specific Populations (8.5), and Clinical Studies (14.4)].

In the WHIMS estrogen plus progestin ancillary study, a population of 4,532 postmenopausal women 65 to 79 years of age was randomized to daily CE (0.625 mg) plus MPA (2.5 mg) or placebo.

After an average follow-up of 4 years, 40 women in the CE plus MPA group and 21 women in the placebo group were diagnosed with probable dementia. The relative risk of probable dementia for CE plus MPA versus placebo was 2.05 (95 percent CI, 1.21-3.48). The absolute risk of probable dementia for CE plus MPA versus placebo was 45 versus 22 cases per 10,000 women-years^8 [see Use in Specific Populations (8.5), and Clinical Studies (14.4)].

When data from the two populations in the WHIMS estrogen-alone and estrogen plus progestin ancillary studies were pooled as planned in the WHIMS protocol, the reported overall relative risk for probable dementia was 1.76 (95 percent CI, 1.19-2.60). Since both ancillary substudies were conducted in women aged 65 to 79 years, it is unknown whether these findings apply to younger postmenopausal women^8 [see Use in Specific Populations (8.5) and Clinical Studies (14.4)].

5.4 Gallbladder Disease

A 2- to 4-fold increase in the risk of gallbladder disease requiring surgery in postmenopausal women receiving estrogens has been reported.

5.5 Hypercalcemia

Estrogen administration may lead to severe hypercalcemia in women with breast cancer and bone metastases. If hypercalcemia occurs, use of the drug should be stopped and appropriate measures taken to reduce the serum calcium level.

5.6 Visual Abnormalities

Retinal vascular thrombosis has been reported in women receiving estrogens. Discontinue medication pending examination if there is sudden partial or complete loss of vision, or a sudden onset of proptosis, diplopia, or migraine. If examination reveals papilledema or retinal vascular lesions, estrogens should be permanently discontinued.

5.7 Addition of a Progestin When a Woman Has Not Had a Hysterectomy

Studies of the addition of a progestin for 10 or more days of a cycle of estrogen administration, or daily with estrogen in a continuous regimen, have reported a lowered incidence of endometrial hyperplasia than would be induced by estrogen treatment alone. Endometrial hyperplasia may be a precursor to endometrial cancer. There are, however, possible risks that may be associated with the use of progestins with estrogens compared to estrogen-alone regimens. These include an increased risk of breast cancer.

5.8 Elevated Blood Pressure

In a small number of case reports, substantial increases in blood pressure have been attributed to idiosyncratic reactions to estrogens. In a large, randomized, placebo-controlled clinical trial, a generalized effect of estrogen therapy on blood pressure was not seen.

5.9 Hypertriglyceridemia

In women with pre-existing hypertriglyceridemia, estrogen therapy may be associated with elevations of plasma triglycerides leading to pancreatitis. Consider discontinuation of treatment if pancreatitis occurs.

5.10 Hepatic Impairment and/or a Past History of Cholestatic Jaundice

Estrogens may be poorly metabolized in women with impaired liver function. For women with a history of cholestatic jaundice associated with past estrogen use or with pregnancy, caution should be exercised and in the case of recurrence, medication should be discontinued.

5.11 Hypothyroidism

Estrogen administration leads to increased thyroid-binding globulin (TBG) levels. Women with normal thyroid function can compensate for the increased TBG by making more thyroid hormone, thus maintaining free T4 and T3 serum concentrations in the normal range. Women dependent on thyroid hormone replacement therapy who are also receiving estrogens may require increased doses of their thyroid replacement therapy. These women should have their thyroid function monitored in order to maintain their free thyroid hormone levels in an acceptable range.

5.12 Fluid Retention

Estrogens may cause some degree of fluid retention. Women with conditions that might be influenced by this factor, such as cardiac or renal impairment, warrant careful observation when estrogen-alone is prescribed.

5.13 Hypocalcemia

Estrogen therapy should be used with caution in women with hypoparathyroidism as estrogen-induced hypocalcemia may occur.

5.14 Exacerbation of Endometriosis

A few cases of malignant transformation of residual endometrial implants have been reported in women treated post-hysterectomy with estrogen-alone therapy. For women known to have residual endometriosis post-hysterectomy, the addition of progestin should be considered.

5.15 Hereditary Angioedema

Exogenous estrogens may exacerbate symptoms of angioedema in women with hereditary angioedema.

5.16 Exacerbation of Other Conditions

Estrogen therapy may cause an exacerbation of asthma, diabetes mellitus, epilepsy, migraine, porphyria, systemic lupus erythematosus and hepatic hemangiomas, and should be used with caution in women with these conditions.

5.17 Laboratory Tests

Serum follicle stimulating hormone (FSH) and estradiol levels have not been shown to be useful in the management of moderate to severe vasomotor symptoms and moderate to severe vulvar and vaginal atrophy due to menopause.

5.18 Drug-Laboratory Test Interactions

Accelerated prothrombin time, partial thromboplastin time, and platelet aggregation time; increased platelet count; increased factors II, VII antigen, VIII antigen, VIII coagulant activity, IX, X, XII, VII-X complex, II-VII-X complex, and beta-thromboglobulin; decreased levels of antifactor Xa and antithrombin III, decreased antithrombin III activity; increased levels of fibrinogen and fibrinogen activity; increased plasminogen antigen and activity.

Increased TBG levels leading to increased circulating total thyroid hormone levels as measured by protein-bound iodine (PBI), T4 levels (by column or by radioimmunoassay) or T3 levels by radioimmunoassay. T3 resin uptake is decreased, reflecting the elevated TBG. Free T4 and free T3 concentrations are unaltered. Women on thyroid replacement therapy may require higher doses of thyroid hormone.

Other binding proteins may be elevated in serum, for example, corticosteroid binding globulin (CBG), sex hormone-binding globulin (SHBG), leading to increased total circulating corticosteroids and sex steroids, respectively. Free hormone concentrations, such as testosterone and estradiol, may be decreased. Other plasma proteins may be increased (angiotensinogen/renin substrate, alpha-1-antitrypsin, ceruloplasmin).

Increased plasma high-density lipoprotein (HDL) and HDL2 cholesterol subfraction concentrations, reduced low-density lipoprotein (LDL) cholesterol concentration, increased triglycerides levels.

Impaired glucose tolerance.

5.19 Vaginal Use and Expulsion

Femring may not be suitable for women with conditions that make the vagina more susceptible to vaginal irritation or ulceration, or make expulsions more likely, such as narrow vagina, vaginal stenosis, vaginal infection, cervical prolapse, rectoceles and cystoceles. If local treatment of a vaginal infection is required, Femring can remain in place during treatment.

6 ADVERSE REACTIONS

The following serious adverse reactions are discussed elsewhere in the labeling:

- Cardiovascular Disorders [see Boxed Warning, Warnings and Precautions (5.1)].
- Malignant Neoplasms [see Boxed Warning, Warnings and Precautions (5.2)].

6.1 Clinical Trials Experience

Because clinical trials are conducted under widely varying conditions, adverse reaction rates observed in the clinical trials of a drug cannot be directly compared to rates in the clinical trials of another drug and may not reflect the rates observed in practice.

In a 13-week clinical trial that included 225 postmenopausal women treated with Femring and 108 women treated with placebo vaginal rings, adverse reactions that occurred at a rate of ≥ 2 percent are summarized in Table 1.

Table 1. Incidence of Adverse Reactions Occurring in ≥ 2 Percent of Subjects Presented in Descending Frequency of Preferred Term
Adverse Event | Placebo (n = 108) | Estradiol 0.05 mg/day (n = 113) | Estradiol 0.10 mg/day (n = 112)
 | n (percent) | n (percent) | n (percent)
Headache (NOS) | 10 (9.3) | 8 (7.1) | 11 (9.8)
Intermenstrual Bleeding | 2 (1.9) | 9 (8.0) | 11 (9.8)
Vaginal Candidiasis | 3 (2.8) | 7 (6.2) | 12 (10.7)
Breast Tenderness | 2 (1.9) | 7 (6.2) | 12 (10.7)
Back Pain | 4 (3.7) | 7 (6.2) | 4 (3.6)
Abdominal Distension | 3 (2.8) | 8 (7.1) | 3 (2.7)
Sinusitis (NOS) | 2 (1.9) | 2 (1.8) | 4 (3.6)
Uterine Pain | 1 (0.9) | 2 (1.8) | 5 (4.5)
Urinary Tract Infection (NOS) | 2 (1.9) | 1 (0.9) | 4 (3.6)
AE = adverse event; NOS = not otherwise specified

6.2 Postmarketing Experience

1. A few cases of toxic shock syndrome (TSS) have been reported in women using vaginal rings. TSS is a rare, but serious disease that may cause death. Warning signs of TSS include fever, nausea, vomiting, diarrhea, muscle pain, dizziness, faintness, or a sunburn-rash on face and body.
2. Cases of ring adherence to the vaginal or bladder wall, making ring removal difficult, have been reported in women using vaginal rings and may require surgical removal of the device. Women should be carefully evaluated for vaginal or bladder wall ulceration or erosion. Cases of vaginal erosion and vaginal ulceration have been reported with other estradiol vaginal rings. If an ulceration or erosion has occurred, consideration should be given to leaving the ring out and not replacing it until healing is complete to prevent the ring from adhering to the vaginal tissue.
3. A few cases of bowel obstruction associated with vaginal ring use have been reported. Persistent abdominal complaints consistent with obstruction should be carefully evaluated.
4. A few cases of inadvertent ring insertion into the urinary bladder, which may require surgical removal, have been reported for women using vaginal rings. Persistent unexplained urinary symptoms should be carefully evaluated.

The following additional adverse reactions have been identified during post-approval use of Femring. Because these reactions are reported voluntarily from a population of uncertain size, it is not always possible to reliably estimate their frequency or establish a causal relationship to drug exposure.

Genitourinary system
Uterine cancer, vaginal hemorrhage, ovarian cyst, irregular menstruation, metrorrhagia, menorrhagia, dysmenorrhea, uterine enlargement.

Breasts
Breast cancer, fibrocystic breast disease, breast disorder, breast mass, breast enlargement, breast pain, nipple pain, breast discharge.

Cardiovascular
Chest pain, increased blood pressure, irregular heart rate, pulmonary embolism, cerebrovascular accident (stroke), hemiparesis, transient ischemic attack, thrombosis.

Gastrointestinal
Abdominal pain, pancreatitis, cholecystitis, cholelithiasis, vomiting.

Skin
Generalized erythema, erythema multiforme, erythema nodosum, rash, hirsutism, pruritis.

Eyes
Blindness, contact lens intolerance.

Central Nervous System
Dizziness, headache, depression, nervousness, mood disturbances, irritability.

Miscellaneous
Medical device complication, back pain, angioedema, weight increased/decreased, edema, libido increased/decreased, urticaria, hypersensitivity, anaphylaxis.

7 DRUG INTERACTIONS

No drug interaction studies have been conducted for Femring.

7.1 Metabolic Interactions

In vitro and in vivo studies have shown that estrogens are metabolized partially by cytochrome P450 3A4 (CYP3A4). Therefore, inducers or inhibitors of CYP3A4 may affect estrogen drug metabolism. Inducers of CYP3A4 such as St. John’s wort (Hypericum perforatum) preparations, phenobarbital, carbamazepine and rifampin may decrease the plasma concentration of estrogens, possibly resulting in a decrease in therapeutic effects and/or changes in the uterine bleeding profile. Inhibitors of CYP3A4 such as erythromycin, clarithromycin, ketoconazole, itraconazole, ritonavir and grapefruit juice may increase the plasma concentration of estrogens and may result in side effects.

8 USE IN SPECIFIC POPULATIONS

8.1 Pregnancy

Femring should not be used during pregnancy [see Contraindications (4)]. There appears to be little or no increased risk of birth defects in children born to women who have used estrogens and progestins as an oral contraceptive inadvertently during early pregnancy.

8.3 Nursing Mothers

Femring should not be used during lactation. Estrogen administration to nursing women has been shown to decrease the quantity and quality of the breast milk. Detectable amounts of estrogens have been identified in the breast milk of women receiving estrogen-alone therapy. Caution should be exercised when Femring is administered to a nursing woman.

8.4 Pediatric Use

Femring is not indicated in children. Clinical studies have not been conducted in the pediatric population.

8.5 Geriatric Use

There have not been sufficient numbers of geriatric women involved in clinical studies utilizing Femring to determine whether those over 65 years of age differ from younger subjects in their response to Femring.

The Women’s Health Initiative Studies

In the WHI estrogen-alone substudy (daily CE [0.625 mg]-alone versus placebo), there was a higher relative risk of stroke in women greater than 65 years of age [see Clinical Studies (14.2)].

In the WHI estrogen plus progestin substudy (daily CE [0.625 mg] plus MPA [2.5 mg] versus placebo), there was a higher relative risk of nonfatal stroke and invasive breast cancer in women greater than 65 years of age [see Clinical Studies (14.2)].

The Women’s Health Initiative Memory Study

In the WHIMS ancillary studies of postmenopausal women 65 to 79 years of age, there was an increased risk of developing probable dementia in women receiving estrogen-alone or estrogen plus progestin when compared to placebo [see Warnings and Precautions (5.3), and Clinical Studies (14.4)].

Since both ancillary studies were conducted in women 65 to 79 years of age, it is unknown whether these findings apply to younger postmenopausal women^8 [see Warnings and Precautions (5.3), and Clinical Studies (14.4)].

8.6 Renal Impairment

The effect of renal impairment on the pharmacokinetics of Femring has not been studied.

8.7 Hepatic Impairment

The effect of hepatic impairment on the pharmacokinetics of Femring has not been studied.

10 OVERDOSAGE

Overdosage of estrogen may cause nausea, vomiting, breast tenderness, dizziness, abdominal pain, drowsiness and fatigue, and withdrawal bleeding may occur in women. Treatment of overdose consists of discontinuation of Femring with institution of appropriate symptomatic care.

11 DESCRIPTION

Femring (estradiol acetate vaginal ring) is an off-white, soft, flexible ring with a central core containing estradiol acetate.

Femring is made of cured silicone elastomer composed of dimethyl polysiloxane silanol, silica (diatomaceous earth), normal propyl orthosilicate, stannous octoate; barium sulfate and estradiol acetate. The rings have the following dimensions: outer diameter 56 mm, cross-sectional diameter 7.6 mm, core diameter 2 mm.

Femring is available in two strengths: Femring 0.05 mg/day has a central core that contains 12.4 mg of estradiol acetate, which releases at a rate equivalent to 0.05 mg of estradiol per day for 3 months. Femring 0.10 mg/day has a central core that contains 24.8 mg of estradiol acetate, which releases at a rate equivalent to 0.10 mg of estradiol per day for 3 months.

Estradiol acetate is chemically described as estra-1,3,5(10)-triene-3,17β-diol-3-acetate. The molecular formula of estradiol acetate is C20H26O3 and the molecular weight of estradiol acetate is 314.42.

12 CLINICAL PHARMACOLOGY

12.1 Mechanism of Action

Endogenous estrogens are largely responsible for the development and maintenance of the female reproductive system and secondary sexual characteristics. Although circulating estrogens exist in a dynamic equilibrium of metabolic interconversions, estradiol is the principal intracellular human estrogen and is substantially more potent than its metabolites, estrone and estriol, at the receptor level.

The primary source of estrogen in normally cycling adult women is the ovarian follicle, which secretes 70 to 500 mcg of estradiol daily, depending on the phase of the menstrual cycle. After menopause, most endogenous estrogen is produced by conversion of androstenedione, which is secreted by the adrenal cortex, to estrone in the peripheral tissues. Thus, estrone and the sulfate conjugated form, estrone sulfate, are the most abundant circulating estrogens in postmenopausal women.

Estrogens act through binding to nuclear receptors in estrogen-responsive tissues. To date, two estrogen receptors have been identified. These vary in proportion from tissue to tissue.

Circulating estrogens modulate the pituitary secretion of the gonadotropins, luteinizing hormone (LH) and FSH through a negative feedback mechanism. Estrogens act to reduce the elevated levels of these hormones seen in postmenopausal women.

12.2 Pharmacodynamics

There are no pharmacodynamic data for Femring.

12.3 Pharmacokinetics

Absorption

Estradiol acetate is hydrolyzed to estradiol which is absorbed through the vaginal mucosa as evidenced by the mean time to maximum concentration (tmax) for estradiol of about 1 hour (range 0.25 to 1.5 hrs). After achieving the Cmax the estradiol concentration starts declining during the first 24 to 48 hours and then at a relatively constant rate for the remainder of the 3-month dosing interval (see Figure 1 for results from rings stored for 16 months). In vitro studies have shown that this initial release is higher as the rings age upon storage.

Figure 1. Mean serum estradiol concentrations following multiple dose administration of Femring (0.05 mg/day estradiol) (second dose administered at 13 weeks) (inset: mean (±SD) of serum concentration-time profile for dose 1 from 0-24 hours)

Following administration of Femring (0.05 mg/day estradiol), average serum estradiol concentration was 40.6 pg/mL; the corresponding apparent in vivo estradiol delivery rate was 0.052 mg/day. Following administration of Femring (0.10 mg/day estradiol), average serum estradiol concentration was 76 pg/mL; apparent in vivo delivery rate was 0.097 mg/day. Results are summarized in Table 2 below.

Table 2. Summary of Mean (Percent RSD)* Pharmacokinetic Parameters for Femring
Dose (as estradiol) |  | Number of subjects | Cmax (pg/mL) | Tmax (hour) | Cavg (pg/mL)
 | Estradiol^1 | 25 | 1129 (25) | 0.9 (41) | 40.6 (26)
0.05 mg/day | Estrone^1 | 25 | 141 (25) | 6.2 (84) | 35.9 (21)
 | Estrone sulfate^1 | 25 | 2365 (44) | 9.3 (39) | 494.6 (48)
 | Estradiol^2 | 12 | 1665 (23) | 0.7 (90) | --^4
0.10 mg/day | Estradiol^3 | 11 | -- | -- | 76.0 (24)
 | Estrone^3 | 11 | -- | -- | 45.7 (25)
* Relative Standard Deviation, ^1Study 1, ^2Study 2, ^3Study 3, ^4-- Not determined

Consistent with the avoidance of first pass metabolism achieved by vaginal estradiol administration, serum estradiol concentrations were slightly higher than estrone concentrations.

Distribution

The distribution of exogenous estrogens is similar to that of endogenous estrogens. Estrogens are widely distributed in the body and are generally found in higher concentrations in the sex hormone target organs. Estrogens circulate in the blood largely bound to SHBG and albumin.

Metabolism

Exogenous estrogens are metabolized in the same manner as endogenous estrogens. Circulating estrogens exist in a dynamic equilibrium of metabolic interconversions. These transformations take place mainly in the liver. Estradiol is converted reversibly to estrone, and both can be converted to estriol, which is a major urinary metabolite. Estrogens also undergo enterohepatic recirculation via sulfate and glucuronide conjugation in the liver, biliary secretion of conjugates into the intestine, and hydrolysis in the intestine followed by reabsorption. In postmenopausal women, a significant proportion of the circulating estrogens exist as sulfate conjugates, especially estrone sulfate, which serves as a circulating reservoir for the formation of more active estrogens.

Excretion

Estradiol, estrone, and estriol are excreted in the urine along with glucuronide and sulfate conjugates.

The estradiol apparent elimination half-life value is 21 to 26 hours.

Use in Specific Populations

No pharmacokinetic studies were conducted with Femring in specific populations, including women with renal or hepatic impairment.

13 NONCLINICAL TOXICOLOGY

13.1 Carcinogenesis, Mutagenesis, Impairment of Fertility

Long-term continuous administration of natural and synthetic estrogens in certain animal species increases the frequency of carcinomas of the breast, uterus, cervix, vagina, testis, and liver.

Estradiol acetate was assayed for mutation in four histidine-requiring strains of Salmonella typhimurium and in one tryptophan-requiring strain of Escherichia coli. Estradiol acetate did not induce mutations in any of the bacterial strains tested under the conditions employed.

14 CLINICAL STUDIES

14.1 Effects on Vasomotor Symptoms

A 13-week double-blind, placebo-controlled clinical trial was conducted to evaluate the efficacy of 2 doses of the vaginal ring in the treatment of moderate to severe vasomotor symptoms in 333 postmenopausal women between 29 and 85 years of age (mean age 51.7 years, 77 percent were Caucasian) who had at least 7 moderate to severe hot flushes daily or at least 56 moderate to severe hot flushes per week before randomization. Patients were randomized to receive either placebo, Femring 0.05 mg/day or Femring 0.10 mg/day. Femring 0.05 mg/day and Femring 0.10 mg/day were shown to be statistically better than placebo at weeks 4 and 12 for relief of both the frequency and severity of moderate to severe vasomotor symptoms. Frequency results are shown in Table 3. Severity results are shown in Table 4.

Table 3. Mean Change from Baseline in the Number of Moderate to Severe Vasomotor Symptoms per Week – ITT Population, LOCF
Visit | Placebo (n = 105) | Estradiol 0.05 mg/day (n = 111) | Estradiol 0.10 mg/day (n = 109)
Baseline [1]
Mean (SD) | 83.62 (60.42) | 73.83 (24.53) | 75.11 (25.44)
Week 4
Mean (SD) | 51.14 (51.19) | 21.59* (27.76) | 11.37* (19.43)
Mean Change from Baseline (SD) | -32.48 (46.25) | -52.24* (32.92) | -63.75* (26.68)
p value vs. Placebo (95 percent CI) [2] | - | <0.001 (-30.7, -8.8) | <0.001 (-42.2, -20.3)
Week 12
Mean (SD) | 42.21 (41.13) | 15.48* (25.42) | 8.25* (16.58)
Mean Change from Baseline (SD) | -41.41 (65.61) | -58.36* (31.36) | -66.87* (27.44)
p value vs. Placebo (95 percent CI) [2] | - | 0.006 (-30.5, -3.4) | <0.001 (-39.1, -11.8)
*Denotes statistical significance at the 0.050 level.
[1] The baseline number of moderate to severe vasomotor symptoms (MSVS) is the weekly average number of
MSVS during the two weeks between screening and randomization.
[2] p values and confidence intervals are from a two-way ANOVA with factors for treatment and study center for the difference between treatment groups in the mean change from baseline. Confidence intervals are adjusted for multiple comparisons within each timepoint using Dunnett’s method.
ITT = intent to treat; LOCF = last observation carried forward; CI = confidence interval

Table 4. Mean Change from Baseline in the Severity of Moderate to Severe Vasomotor Symptoms per Week – ITT Population, LOCF
Visit | Placebo (n = 105) | Estradiol 0.05 mg/day (n = 111) | Estradiol 0.10 mg/day (n = 109)
Baseline [1]
Mean (SD) | 2.51 (0.26) | 2.46 (0.23) | 2.48 (0.24)
Week 4
Mean (SD) | 2.23 (0.71) | 1.67* (1.07) | 1.15* (1.14)
Mean Change from Baseline (SD) | -0.28 (0.69) | - 0.79* (1.08) | -1.33* (1.10)
p value vs. Placebo (95 percent CI) [2] | - | <0.001 (-0.8, -0.2) | <0.001 (-1.3, -0.8)
Week 12
Mean (SD) | 2.00 (0.96) | 1.41* (1.17) | 0.92* (1.09)
Mean Change from Baseline (SD) | -0.51 (0.94) | -1.06* (1.16) | -1.56* (1.06)
p value vs. Placebo (95 percent CI) [2] | - | <0.001 (-0.9, -0.2) | <0.001 (-1.4, -0.7)
*Denotes statistical significance at the 0.050 level.
[1] The baseline severity of moderate to severe vasomotor symptoms (MSVS) is the average severity of MSVS during the two weeks between screening and randomization.
[2] p values and confidence intervals are from a two-way ANOVA with factors for treatment and study center for the difference between treatment groups in the mean change from baseline. Confidence intervals are adjusted for multiple comparisons within each timepoint using Dunnett’s method.
ITT = intent to treat; LOCF = last observation carried forward; CI = confidence interval

14.2 Effects on Vulvar and Vaginal Atrophy

In the same 13-week clinical trial, vaginal superficial cells increased by a mean of 16.0 percent and 18.9 percent for Femring 0.05 mg/day and Femring 0.10 mg/day, respectively, as compared to 1.11 percent for placebo at week 13. A corresponding reduction in parabasal cells was observed at week 13. Vaginal pH decreased for Femring 0.05 mg/day and Femring 0.10 mg/day by a mean of 0.73 and 0.60, respectively, compared to a mean decrease of 0.25 in the placebo group.

14.3 Women’s Health Initiative Studies

The WHI enrolled approximately 27,000 predominantly healthy postmenopausal women in two substudies to assess the risks and benefits of daily oral CE (0.625 mg)-alone or in combination with MPA (2.5 mg) compared to placebo in the prevention of certain chronic diseases. The primary endpoint was the incidence of CHD (defined as nonfatal MI, silent MI and CHD death), with invasive breast cancer as the primary adverse outcome. A “global index” included the earliest occurrence of CHD, invasive breast cancer, stroke, PE, endometrial cancer (only in the CE plus MPA substudy), colorectal cancer, hip fracture, or death due to other cause. These substudies did not evaluate the effects of CE-alone or CE plus MPA on menopausal symptoms.

WHI Estrogen-Alone Substudy

The WHI estrogen-alone substudy was stopped early because an increased risk of stroke was observed, and it was deemed that no further information would be obtained regarding the risks and benefits of estrogen-alone in predetermined primary endpoints.

Results of the estrogen-alone substudy, which included 10,739 women (average 63 years of age, range 50 to 79; 75.3 percent White, 15.1 percent Black, 6.1 percent Hispanic, 3.6 percent Other), after an average follow-up of 7.1 years, are presented in Table 5.

Table 5. Relative and Absolute Risk Seen in the Estrogen-Alone Substudy of WHIa
Event |  | Relative Risk CE vs. Placebo (95 percent nCIb) | CE n = 5,310 | Placebo n = 5,429
 |  |  | Absolute Risk per 10,000 Women-Years
CHD eventsc |  | 0.95 (0.78-1.16) | 54 | 57
 | Non-fatal MIc | 0.91 (0.73-1.14) | 40 | 43
 | CHD deathc | 1.01 (0.71-1.43) | 16 | 16
All strokesc |  | 1.33 (1.05-1.68) | 45 | 33
 | Ischemic strokec | 1.55 (1.19-2.01) | 38 | 25
Deep vein thrombosisc,d |  | 1.47 (1.06-2.06) | 23 | 15
Pulmonary embolismc |  | 1.37 (0.90-2.07) | 14 | 10
Invasive breast cancerc |  | 0.80 (0.62-1.04) | 28 | 34
Colorectal cancerc |  | 1.08 (0.75-1.55) | 17 | 16
Hip fracturec |  | 0.65 (0.45-0.94) | 12 | 19
Vertebral fracturesc,d |  | 0.64 (0.44-0.93) | 11 | 18
Lower arm/wrist fracturesc,d |  | 0.58 (0.47-0.72) | 35 | 59
Total fracturesc,d |  | 0.71 (0.64-0.80) | 144 | 197
Deaths due to other causese,f |  | 1.08 (0.88-1.32) | 53 | 50
Overall Mortalityc,d |  | 1.04 (0.88-1.22) | 79 | 75
Global Indexg |  | 1.02 (0.92-1.13) | 206 | 201
aAdapted from numerous WHI publications. WHI publications can be viewed at www.nhlbi.nih.gov/whi.
bNominal confidence intervals unadjusted for multiple looks and multiple comparisons.
cResults are based on centrally adjudicated data for an average follow-up of 7.1 years.
dNot included in “global index”.
eResults are based on an average follow-up of 6.8 years.
fAll deaths, except from breast or colorectal cancer, definite or probable CHD, PE or cerebrovascular disease.
gA subset of the events was combined in a “global index” defined as the earliest occurrence of CHD events, invasive breast cancer, stroke, PE, colorectal cancer, hip fracture, or death due to other causes.

For those outcomes included in the WHI “global index” that reached statistical significance, the absolute excess risk per 10,000 women-years in the group treated with CE-alone were 12 more strokes, while the absolute risk reduction per 10,000 women-years was 7 fewer hip fractures. ^9 The absolute excess risk of events included in the “global index” was a non-significant 5 events per 10,000 women-years. There was no difference between the groups in terms of all-cause mortality.

No overall difference for primary CHD events (nonfatal MI, silent MI and CHD death) and invasive breast cancer incidence in women receiving CE-alone compared with placebo was reported in final centrally adjudicated results from the estrogen-alone substudy, after an average follow-up of 7.1 years. See Table 5.

Centrally adjudicated results for stroke events from the estrogen-alone substudy, after an average follow-up of 7.1 years, reported no significant difference in distribution of stroke subtype or severity, including fatal strokes, in women receiving CE-alone compared to placebo. Estrogen-alone therapy increased the risk of ischemic stroke, and this excess was present in all subgroups of women examined.^10 See Table 5.

Timing of the initiation of estrogen-alone therapy relative to the start of menopause may affect the overall risk benefit profile. The WHI estrogen-alone substudy stratified by age, showed in women 50 to 59 years of age, a non-significant trend toward reduced risk for CHD [hazard ratio (HR) 0.63 (95 percent CI, 0.36-1.09)] and overall mortality [HR 0.71 (95 percent CI, 0.46-1.11)].

WHI Estrogen Plus Progestin Substudy

The WHI estrogen plus progestin substudy was stopped early. According to the predefined stopping rule, after an average follow-up of 5.6 years of treatment, the increased risk of breast cancer and cardiovascular events exceeded the specified benefits included in the “global index”. The absolute excess risk of events included in the “global index” was 19 per 10,000 women-years.

For those outcomes included in the WHI “global index” that reached statistical significance after 5.6 years of follow-up, the absolute excess risks per 10,000 women-years in the group treated with CE plus MPA were 7 more CHD events, 8 more strokes, 10 more PEs, and 8 more invasive breast cancers, while the absolute risk reductions per 10,000 women-years were 6 fewer colorectal cancers and 5 fewer hip fractures.

Results of the CE plus MPA substudy, which included 16,608 women (average 63 years of age, range 50 to 79; 83.9 percent White, 6.8 percent Black, 5.4 percent Hispanic, 3.9 percent Other) are presented in Table 6. These results reflect centrally adjudicated data after an average follow-up of 5.6 years.

Table 6. Relative and Absolute Risk Seen in the Estrogen Plus Progestin Substudy of WHI at an Average of 5.6 Yearsa,b
Event | Relative Risk CE/MPA vs. Placebo (95% nCIc) | CE/MPA n = 8,506 | Placebo n = 8,102
 |  | Absolute Risk per 10,000 Women-Years
CHD events | 1.23 (0.99-1.53) | 41 | 34
Non-fatal MI | 1.28 (1.00-1.63) | 31 | 25
CHD death | 1.10 (0.70-1.75) | 8 | 8
All strokes | 1.31 (1.03-1.68) | 33 | 25
Ischemic stroke | 1.44 (1.09-1.90) | 26 | 18
Deep vein thrombosisd | 1.95 (1.43-2.67) | 26 | 13
Pulmonary embolism | 2.13 (1.45-3.11) | 18 | 8
Invasive breast cancere | 1.24 (1.01-1.54) | 41 | 33
Colorectal cancer | 0.61 (0.42-0.87) | 10 | 16
Endometrial cancerd | 0.81 (0.48-1.36) | 6 | 7
Cervical cancerd | 1.44 (0.47-4.42) | 2 | 1
Hip fracture | 0.67 (0.47-0.96) | 11 | 16
Vertebral fracturesd | 0.65 (0.46-0.92) | 11 | 17
Lower arm/wrist fracturesd | 0.71 (0.59-0.85) | 44 | 62
Total fracturesd | 0.76 (0.69-0.83) | 152 | 199
Overall Mortalityc,f | 1.00 (0.83-1.19) | 52 | 52
Global Indexg | 1.13 (1.02-1.25) | 184 | 165
aAdapted from numerous WHI publications. WHI publications can be viewed at www.nhlbi.nih.gov/whi.
bResults are based on centrally adjudicated data.
cNominal confidence intervals unadjusted for multiple looks and multiple comparisons.
dNot included in “global index”.
eIncludes metastatic and non-metastatic breast cancer with the exception of in situ cancer.
fAll deaths, except from breast or colorectal cancer, definite or probable CHD, PE or cerebrovascular disease.
gA subset of the events was combined in a “global index” defined as the earliest occurrence of CHD events, invasive breast cancer, stroke, PE, colorectal cancer, hip fracture, or death due to other causes.

Timing of initiation of estrogen plus progestin therapy relative to the start of menopause may affect the overall risk benefit profile. The WHI estrogen plus progestin substudy stratified by age showed in women 50 to 59 years of age a non-significant trend toward reduced risk for overall mortality [HR 0.69 (95 percent CI, 0.44-1.07)].

14.4 Women’s Health Initiative Memory Study

The WHIMS estrogen-alone ancillary study of WHI enrolled 2,947 predominantly healthy hysterectomized postmenopausal women 65 to 79 years of age and older (45 percent were 65 to 69 years of age; 36 percent were 70 to 74 years of age; 19 percent were 75 years of age and older) to evaluate the effects of daily CE (0.625 mg)-alone on the incidence of probable dementia (primary outcome) compared to placebo.

After an average follow-up of 5.2 years, the relative risk of probable dementia for CE-alone versus placebo was 1.49 (95 percent CI, 0.83-2.66). The absolute risk of probable dementia for CE-alone versus placebo was 37 versus 25 cases per 10,000 women-years. Probable dementia as defined in this study included Alzheimer’s disease (AD), vascular dementia (VaD) and mixed types (having features of both AD and VaD). The most common classification of probable dementia in the treatment group and the placebo group was AD. Since the ancillary study was conducted in women 65 to 79 years of age, it is unknown whether these findings apply to younger postmenopausal women [see Warnings and Precautions (5.3), and Use in Specific Populations (8.5)].

The WHIMS estrogen plus progestin ancillary study of WHI enrolled 4,532 predominantly healthy postmenopausal women 65 years of age and older (47 percent were 65 to 69 years of age, 35 percent were 70 to 74 years of age, and 18 percent were 75 years of age and older) to evaluate the effects of CE (0.625 mg) plus MPA (2.5 mg) on the incidence of probable dementia (primary outcome) compared to placebo.

After an average follow-up of 4 years, the relative risk of probable dementia for CE plus MPA versus placebo was 2.05 (95 percent CI, 1.21-3.48). The absolute risk of probable dementia for CE plus MPA versus placebo was 45 versus 22 per 10,000 women-years. Probable dementia as defined in this study included AD, VaD and mixed types (having features of both AD and VaD). The most common classification of probable dementia in the treatment group and the placebo group was AD. Since the substudy was conducted in women 65 to 79 years of age, it is unknown whether these findings apply to younger postmenopausal women [see Warnings and Precautions (5.3), and Use in Specific Populations (8.5)].

When data from the two populations were pooled as planned in the WHIMS protocol, the reported overall relative risk for probable dementia was 1.76 (95 percent CI, 1.19-2.60). Differences between groups became apparent in the first year of treatment. It is unknown whether these findings apply to younger postmenopausal women [see Warnings and Precautions (5.3), and Use in Specific Populations (8.5)].

15 REFERENCES

1. Rossouw JE, et al. Postmenopausal Hormone Therapy and Risk of Cardiovascular Disease by Age and Years Since Menopause. JAMA. 2007;297:1465-1477.
2. Hsia J, et al. Conjugated Equine Estrogens and Coronary Heart Disease. Arch Int Med. 2006;166:357-365.
3. Curb JD, et al. Venous Thrombosis and Conjugated Equine Estrogen in Women Without a Uterus. Arch Int Med. 2006;166:772-780.
4. Cushman M, et al. Estrogen Plus Progestin and Risk of Venous Thrombosis. JAMA. 2004;292:1573-1580.
5. Stefanick ML, et al. Effects of Conjugated Equine Estrogens on Breast Cancer and Mammography Screening in Postmenopausal Women With Hysterectomy. JAMA. 2006;295:1647-1657.
6. Chlebowski RT, et al. Influence of Estrogen Plus Progestin on Breast Cancer and Mammography in Healthy Postmenopausal Women. JAMA. 2003;289:3234-3253.
7. Anderson GL, et al. Effects of Estrogen Plus Progestin on Gynecologic Cancers and Associated Diagnostic Procedures. JAMA. 2003;290:1739-1748.
8. Shumaker SA, et al. Conjugated Equine Estrogens and Incidence of Probable Dementia and Mild Cognitive Impairment in Postmenopausal Women. JAMA. 2004;291:2947-2958.
9. Jackson RD, et al. Effects of Conjugated Equine Estrogen on Risk of Fractures and BMD in Postmenopausal Women With Hysterectomy: Results From the Women’s Health Initiative Randomized Trial. J Bone Miner Res. 2006;21:817-828.
10. Hendrix SL, et al. Effects of Conjugated Equine Estrogen on Stroke in the Women’s Health Initiative. Circulation. 2006;113:2425-2434.

16 HOW SUPPLIED/STORAGE AND HANDLING

16.1 How Supplied

Each Femring (estradiol acetate vaginal ring) is individually packaged in a pouch consisting of one side medical grade paper and the other side polyester/polyethylene laminate.

N 72495-201-05 Femring 0.05 mg/day (estradiol acetate vaginal ring) is available in single units.
N 72495-202-10 Femring 0.10 mg/day (estradiol acetate vaginal ring) is available in single units.

16.2 Storage and Handling

Store at 20º C to 25º C (68º F to 77º F); excursions permitted to -20º C to 40º C (-4º F to 104º F).

Do not store unpouched. Insert immediately upon removal from the protective pouch.

17 PATIENT COUNSELING INFORMATION

See FDA-approved patient labeling (Patient Information and Instructions for Use).

17.1 Vaginal Bleeding

Inform postmenopausal women of the importance of reporting abnormal vaginal bleeding to their healthcare provider as soon as possible [see Warnings and Precautions (5.2)].

17.2 Possible Serious Adverse Reactions with Estrogen-Alone Therapy

Inform postmenopausal women of possible serious adverse reactions of estrogen-alone therapy including Cardiovascular Disorders, Malignant Neoplasms, and Probable Dementia [see Warnings and Precautions (5.1, 5.2, 5.3)].

17.3 Possible Less Serious but Common Adverse Reactions with Estrogen-Alone Therapy

Inform postmenopausal women of possible less serious but common adverse reactions of estrogen-alone therapy such as headache, breast pain and tenderness, nausea and vomiting.

Contact with blood may cause discoloration of Femring during use. This does not affect the release of the drug. Inform postmenopausal women of the importance of reporting abnormal vaginal bleeding to their healthcare provider as soon as possible.

Manufactured by Millicent Pharma (NI) Limited for
Millicent U.S., Inc, East Hanover, NJ 07936.
Product of United Kingdom.

©2018 Millicent. All rights reserved.

FEMRING® is a registered trademark of Millicent Pharma Limited
Millicent® and its design are trademarks of Millicent Pharma Limited

Patient Information

Femring (fem-ring)
(estradiol acetate vaginal ring)

Read this Patient Information before you start using Femring and each time you get a refill. There may be new information. This information does not take the place of talking to your healthcare provider about your menopausal symptoms or your treatment.

What is the most important information I should know about Femring (an estrogen hormone)?

- Using estrogen-alone may increase your chance of getting cancer of the uterus (womb). Report any unusual vaginal bleeding right away while you are using Femring. Vaginal bleeding after menopause may be a warning sign of cancer of the uterus (womb). Your healthcare provider should check any unusual vaginal bleeding to find out the cause.
- Do not use estrogen-alone to prevent heart disease, heart attacks, strokes or dementia (decline in brain function).
- Using estrogen-alone may increase your chances of getting strokes or blood clots.
- Using estrogen-alone may increase your chance of getting dementia, based on a study of women 65 years of age or older.
- Do not use estrogens with progestins to prevent heart disease, heart attacks, strokes or dementia.
- Using estrogens with progestins may increase your chances of getting heart attacks, strokes, breast cancer, or blood clots.
- Using estrogens with progestins may increase your chance of getting dementia, based on a study of women 65 years of age or older.
- You and your healthcare provider should talk regularly about whether you still need treatment with Femring.

What is Femring?

Femring is a prescription vaginal ring that contains estradiol (an estrogen hormone). Femring should be removed after 90 days of continuous use. If you and your healthcare provider decide you should continue using Femring, a new ring can be inserted in your vagina.

What is Femring used for?

Femring is used after menopause to:

- reduce moderate to severe hot flushes

Estrogens are hormones made by a woman’s ovaries. The ovaries normally stop making estrogens when a woman is between 45 and 55 years old. This drop in body estrogen levels causes the “change of life” or menopause, the end of monthly menstrual periods. Sometimes both ovaries are removed during an operation before natural menopause takes place. The sudden drop in estrogen levels causes “surgical menopause”.
When estrogen levels begin dropping, some women get very uncomfortable symptoms, such as feelings of warmth in the face, neck, and chest, or sudden intense episodes of heat and sweating (“hot flashes” or “hot flushes”). In some women the symptoms are mild, and they will not need to take estrogens. In other women, symptoms can be more severe.

- treat moderate to severe menopausal changes in and around the vagina

You and your healthcare provider should talk regularly about whether you still need treatment with Femring to control these problems. If you use Femring only to treat your menopausal changes in and around your vagina, talk with your healthcare provider about whether a topical vaginal product would be better for you.

You and your healthcare provider should talk regularly about whether you still need treatment with Femring.

Who should not use Femring?

Do not start using Femring if you:

- have unusual vaginal bleeding

Vaginal bleeding after menopause may be a warning sign of cancer of the uterus (womb). Your healthcare provider should check any unusual vaginal bleeding to find out the cause.

- currently have or have had certain cancers

Estrogens may increase the chances of getting certain types of cancers, including cancer of the breast and uterus. If you have or have had cancer, talk with your healthcare provider about whether you should use Femring.

- had a stroke or heart attack
- currently have or have had blood clots
- currently have or have had liver problems
- have been diagnosed with a bleeding disorder
- are allergic to Femring or any of its ingredients
  See the list of ingredients in Femring at the end of this leaflet.
- think you may be pregnant
  Femring is not for pregnant women. If you think you may be pregnant, you should have a pregnancy test and know the results. Do not use Femring if the test is positive and talk to your healthcare provider.

What should I tell my healthcare provider before I use Femring?

Before you use Femring, tell your healthcare provider if you:

- have any unusual vaginal bleeding
  Vaginal bleeding after menopause may be a warning sign of cancer of the uterus (womb). Your healthcare provider should check any unusual vaginal bleeding to find out the cause.
- have any problems with your vagina or cervix (lower end of your womb)
  Your healthcare provider may need to check you more carefully if your cervix, bladder, or rectum have fallen out of their normal position and into the vagina or through the opening of the vagina. This may make it more difficult for you to keep Femring in place in your vagina.
- have any other medical conditions
  Your healthcare provider may need to check you more carefully if you have certain conditions such as asthma (wheezing), epilepsy (seizures), diabetes, migraine, endometriosis, lupus, angioedema (swelling of face and tongue) or problems with your heart, liver, thyroid, kidneys, or have high calcium levels in your blood.
- are going to have surgery or will be on bed rest
  Your healthcare provider will let you know if you need to stop using Femring.
- are breastfeeding
  The hormones in Femring can pass into your breast milk.

Tell your healthcare provider about all the medicines you take, including prescription and nonprescription medicines, vitamins and herbal supplements. Some medicines may affect how Femring works. Femring may also affect how your other medicines work. Keep a list of your medicines and show it to your healthcare provider and pharmacist when you get a new medicine.

How should I use Femring?

For detailed instructions, see the step-by-step instructions for using Femring at the end of this Patient Information.

- Use Femring exactly as your healthcare provider tells you to use it.
- Femring is inserted into your vagina by you.
- Femring should stay in your vagina for 90 days.
- After 90 days Femring should be removed. If you and your healthcare provider decide you should continue using Femring, a new Femring can be inserted.
- You and your healthcare provider should talk regularly (every 3 to 6 months) about the dose of medicine you are using and whether you still need treatment with Femring.

What are the possible problems you may have when using Femring?

- toxic shock syndrome (TSS)
  Toxic shock syndrome is a rare but serious illness caused by a bacterial infection that may cause death. Remove your Femring immediately and call your healthcare provider right away if you have any of the following symptoms:
  - fever
  - nausea or vomiting
  - diarrhea
  - muscle pain
  - dizziness
  - feel faint
  - a sunburn rash on your face or body
- attachment to your vaginal wall
  Contact your healthcare provider right away if you have difficulty removing Femring.
- accidental placement in your bladder

What are the possible side effects of Femring?

Side effects are grouped by how serious they are and how often they happen when you are treated.

Serious, but less common side effects include:

- heart attack
- stroke
- blood clots
- dementia
- breast cancer
- cancer of the lining of the uterus (womb)
- cancer of the ovary
- high blood pressure
- high blood sugar
- gallbladder disease
- liver problems
- changes in your thyroid hormone levels
- enlargement of benign tumors of the uterus (“fibroids”)

Call your healthcare provider right away if you get any of the following warning signs, or any other unusual symptoms that concern you:

- new breast lumps
- unusual vaginal bleeding
- changes in vision or speech
- sudden new severe headaches
- severe pains in your chest or legs with or without shortness of breath, weakness and fatigue

Less serious, but common side effects include:

- headache
- breast tenderness or pain
- irregular vaginal bleeding or spotting
- stomach or abdominal cramps, bloating
- nausea and vomiting
- hair loss
- fluid retention
- vaginal yeast infection
- reactions from inserting Femring such as burning, irritation, and itching

These are not all the possible side effects of Femring. For more information, ask your healthcare provider or pharmacist. Tell your healthcare provider if you have any side effects that bother you or does not go away.

You may report side effects to Millicent at 1-877-810-2101 or to FDA at 1-800-FDA-1088.

What can I do to lower my chances of a serious side effect with Femring?

- Talk with your healthcare provider regularly about whether you should continue using Femring.
- If you have a uterus, talk with your healthcare provider about whether the addition of a progestin is right for you. The addition of a progestin is generally recommended for a woman with a uterus to reduce the chance of getting cancer of the uterus (womb). See your healthcare provider right away if you develop vaginal bleeding while using Femring.
- Have a pelvic exam, breast exam and mammogram (breast x-ray) every year unless your healthcare provider tells you something else.
- If members of your family have had breast cancer or if you have ever had breast lumps or an abnormal mammogram (breast x-ray), you may need to have breast exams more often.
- If you have high blood pressure, high cholesterol (fat in the blood), diabetes, are overweight, or if you use tobacco, you may have a higher chance for getting heart disease.

Ask your healthcare provider for ways of lowering your chances for getting heart disease.

How should I store Femring?

- Store at 68º F to77º F (20º C to 25º C); excursions permitted to -4º F to 104º F (-20º C to 40º C).

KEEP FEMRING and all other medicines out of the reach of children.

General information about safe and effective use of Femring.

Medicines are sometimes prescribed for conditions that are not mentioned in patient information leaflets. Do not use Femring for conditions for which it was not prescribed. Do not give Femring to other people, even if they have the same symptoms you have. It may harm them.

Contact with blood may cause discoloration of Femring during use. This does not affect the way in which Femring releases medicine to control your menopausal symptoms. Call your health care provider right away if you have unusual vaginal bleeding.

This leaflet summarizes the most important information about Femring. If you would like more information, talk with your healthcare provider or pharmacist. You can ask for information about Femring that is written for health professionals. You can get more information by calling the toll free number 1-877-810-2101.

What are the ingredients in Femring?

Active ingredient: estradiol

Inactive ingredients: cured silicone elastomer composed of dimethyl polysiloxane silanol, silica (diatomaceous earth), normal propyl orthosilicate, stannous octoate; and barium sulfate. There are no coloring agents in Femring.

Instructions for Use

Femring (fem-ring)
(estradiol acetate vaginal ring)

Inserting Femring into your vagina:

Step 1. Wash and dry your hands.

Step 2. Remove Femring from the pouch it comes in.

Step 3. Choose the position that is most comfortable for you. For example, lying down or standing with 1 leg up (See Figures A and B).

Step 4. Use your thumb and index finger (pointer finger) to press the sides of the ring together. You may find it easier to insert Femring if you twist it into a figure-eight shape (See Figure C).

Step 5. Use your other hand and hold open the folds of skin around your vagina (See Figure D).

Step 6. Place the tip of the ring in the vaginal opening. Use your index finger to push the folded ring gently into your vagina. Push it up towards your lower back as far as you can (See Figure E).

- If the ring feels uncomfortable, you may not have pushed the ring into your vagina far enough. Use your index finger to push the ring as far as you can into your vagina (See Figure F).

- Femring should now be in your upper vagina (See Figure G). The exact position of Femring in the vagina is not important for it to work.

Step 7. Wash your hands when you are done.

Note: After 90 days, Femring may no longer release enough medicine to control your menopausal symptoms. Your Femring should be removed and replaced with a new one after 90 days of continuous use if you and your healthcare provider have decided that you still need treatment with Femring.

Removing Femring from your vagina:

- Wash and dry your hands.
- Choose the position that is most comfortable for you (See Figures A and B).
- Put a finger into your vagina and hook it through the ring (See Figure H).

- Gently pull downwards and forwards to remove Femring.
- Wrap the used ring in tissue or toilet paper and put it in a trash can.
- Wash your hands.
- Insert another ring now if your healthcare provider has told you to (See Step 1 through Step 7 above under “Inserting Femring into your vagina”).
- If your Femring comes out of your vagina before 90 days, clean it with warm water and put it back in your vagina.
- Femring can come out if:
  - it is not put in far enough
  - you are pushing hard during a bowel movement
  - your vaginal muscles are weak
If Femring comes out often, tell your healthcare provider. Femring may not be right for you.

Call your healthcare provider if you have any problems putting Femring in your vagina or taking it out.

You may leave Femring in place if you need to use medicine for a vaginal infection.

You may leave Femring in place during sex (intercourse). If you take Femring out during intercourse or it comes out, clean it with warm water and put it back in your vagina.

If you lose your Femring, a new Femring should be put in place for 90 days.

Store at 68º F to 77º F (20º C to 25º C); excursions permitted to -4º F to 104º F (-20º C to 40º C).

This Patient Information and Instructions for Use have been approved by the U.S. Food and Drug Administration.

Manufactured by Millicent Pharma (NI) Limited for Millicent U.S., Inc, East Hanover, NJ 07936.

Product of United Kingdom.

© 2018 Millicent. All rights reserved.

FEMRING® is a registered trademark of Millicent Pharma Limited.

Millicent Pharma® and its design are trademarks of Millicent Pharma Limited.

Revised: 11/2023

PRINCIPAL DISPLAY PANEL – 0.05 mg/day Carton Label

NDC 72495-201-05

Femring®
(estradiol acetate vaginal ring)

0.05 mg/day

PRINCIPAL DISPLAY PANEL – 0.05 mg/day Pouch Label

N 72495-201-05

PM00004

Femring®
(estradiol acetate vaginal ring)

0.05 mg/day

(Contains 12.4 mg estradiol acetate to deliver the equivalent of 0.05 mg
estradiol per day for three months.)
Other ingredients: barium sulfate and cured elastomer.

For intravaginal use only.
CONTENTS: 1 VAGINAL RING

Femring® is a registered trademark of
Millicent Pharma Limited

MillicentTM
Pharma

Rx ONLY

PRINCIPAL DISPLAY PANEL – 0.10 mg/day Carton Label

NDC 72495-202-10

Femring®

(estradiol acetate vaginal ring)
0.10 mg/day

PRINCIPAL DISPLAY PANEL – 0.10 mg/day Pouch Label

N 72495-202-10

PM00005

Femring®
(estradiol acetate vaginal ring)

0.10 mg/day

(Contains 24.8 mg estradiol acetate to deliver the equivalent of 0.10 mg
estradiol per day for three months.)
Other ingredients: barium sulfate and cured elastomer.

For intravaginal use only.
CONTENTS: 1 VAGINAL RING

Femring® is a registered trademark of
Millicent Pharma Limited

MillicentTM
Pharma

Rx ONLY